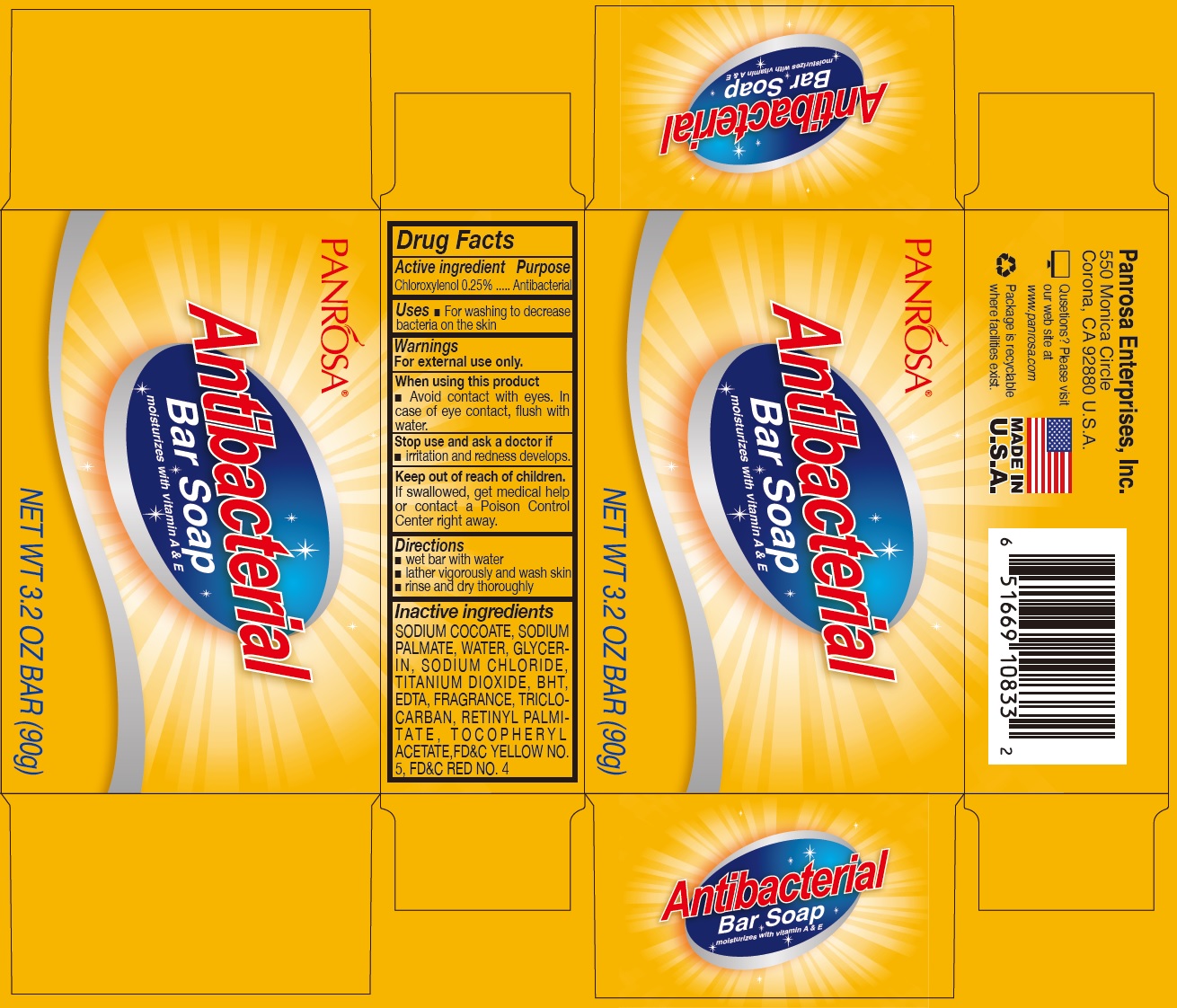 DRUG LABEL: Panrosa Antibacterial Bar
NDC: 50302-014 | Form: SOAP
Manufacturer: Panrosa Enterprises, Inc.
Category: otc | Type: HUMAN OTC DRUG LABEL
Date: 20200702

ACTIVE INGREDIENTS: CHLOROXYLENOL 2.5 mg/1 g
INACTIVE INGREDIENTS: SODIUM COCOATE; SODIUM PALMATE; WATER; GLYCERIN; SODIUM CHLORIDE; TITANIUM DIOXIDE; BUTYLATED HYDROXYTOLUENE; EDETIC ACID; TRICLOCARBAN; VITAMIN A PALMITATE; .ALPHA.-TOCOPHEROL ACETATE; FD&C YELLOW NO. 5; FD&C RED NO. 4

Panrosa Antibacterial Bar Soap

Active ingredient

Chloroxylenol 0.25%

Purpose

Antibacterial

Uses

- For washing to decrease bacteria on the skin

Warnings

For external use only.

When using this product

- Avoid contact with eyes. In case of eye contact, flush with water.

Stop use and ask a doctor if

- irritation and redness develops.

Keep out of reach of children.

If swallowed, get medical help or contact a Poison Control Center right away.

Directions

- wet bar with water
- lather vigorously and wash skin
- rinse and dry thoroughly

Inactive ingredients

SODIUM COCOATE, SODIUM PALMATE, WATER, GLYCERIN, SODIUM CHLORIDE, TITANIUM DIOXIDE, BHT, EDTA, FRAGRANCE, TRICLOCARBAN, RETINYL PALMITATE , TOCOPHERYL ACETATE,FD&C YELLOW NO. 5, FD&C RED NO. 4